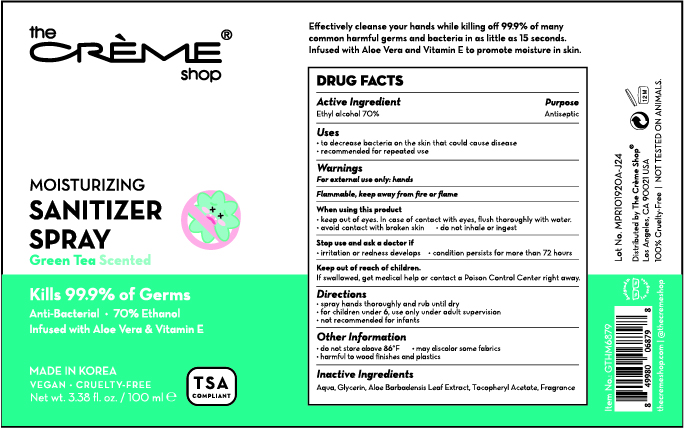 DRUG LABEL: The creme shop MOISTURIZING SANITIZER SRPAY Green Tea Scented
NDC: 74741-1270 | Form: SPRAY
Manufacturer: MPRBRAIN CO.LTD
Category: otc | Type: HUMAN OTC DRUG LABEL
Date: 20201022

ACTIVE INGREDIENTS: ALCOHOL 70 mL/100 mL
INACTIVE INGREDIENTS: ALOE VERA LEAF; GLYCERIN; .ALPHA.-TOCOPHEROL ACETATE; WATER

The creme shop MOISTURIZING SANITIZER SRPAY Green Tea Scented
74741-1270-1
Bottle+Spray